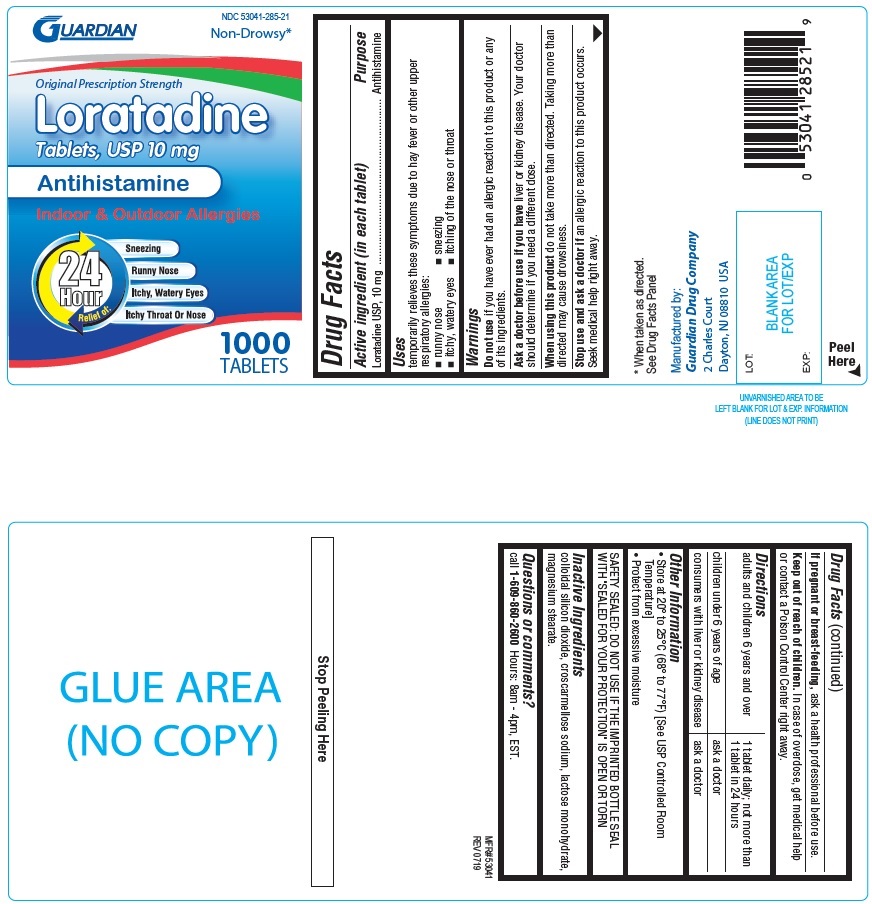 DRUG LABEL: Guardian Loratadine
NDC: 53041-285 | Form: TABLET
Manufacturer: Guardian Drug Company
Category: otc | Type: Human OTC Drug Label
Date: 20190722

ACTIVE INGREDIENTS: LORATADINE 10 mg/1 1
INACTIVE INGREDIENTS: SILICON DIOXIDE; CROSCARMELLOSE SODIUM; LACTOSE MONOHYDRATE; MAGNESIUM STEARATE

Guardian Loratadine Tablets

ACTIVE INGREDIENT (in each tablet)

Loratadine USP, 10mg

PURPOSE

Antihistamine

USE(S)

temporarily relieves these symptoms due to hay fever or other upper respiratory allergies:

- runny nose
- sneezing
- itchy, watery eyes
- itching of the nose or throat

WARNINGS

.

DO NOT USE

if you have ever had an allergic reaction to this product or any of its ingredients.

ASK A DOCTOR BEFORE USE IF YOU HAVE

liver or kidney disease. Your doctor should determine if you need a different dose.

WHEN USING THIS PRODUCT

do not take more than directed. Taking more than directed may cause drowsiness.

STOP USE AND ASK DOCTOR IF

an allergic reaction to this product occurs. Seek medical help right away.

IF PREGNANT OR BREASTFEEDING,

ask a health professional before use.

KEEP OUT OF REACH OF CHILDREN

In case of overdose, get medical help or contact a Poison Control Center right away.

DIRECTIONS

adults and children 6 years and over | 1 tablet daily; not more than 1 tablet in 24 hours
children under 6 years of age | ask a doctor
consumers with liver or kidney disease | ask a doctor

OTHER INFORMATION

- Store at 20o to 25oC (68o to 77oF) [See USP Controlled Room Temperature]
- Protect from excessive moisture

SAFETY SEALED: DO NOT USE IF THE IMPRINTED BOTTLE SEAL WITH "SEALED FOR YOUR PROTECTION" IS OPEN OR TORN

INACTIVE INGREDIENTS

colloidal silicon dioxide, croscarmellose sodium, lactose monohydrate, magnesium stearate

QUESTIONS OR COMMENTS?

call 1-609-860-2600 Hours: 8am-4pm, EST.

PRINCIPAL DISPLAY PANEL

Guardian
NDC 53041-285-21
Non-Drowsy*
Original Prescription Strength
Loratadine
Tablets, USP 10 mg
Antihistamine
Indoor & Outdoor Allergies
24 Hour Relief of:
Sneezing
Runny Nose
Itchy, Watery Eyes
Itchy Throat Or Nose